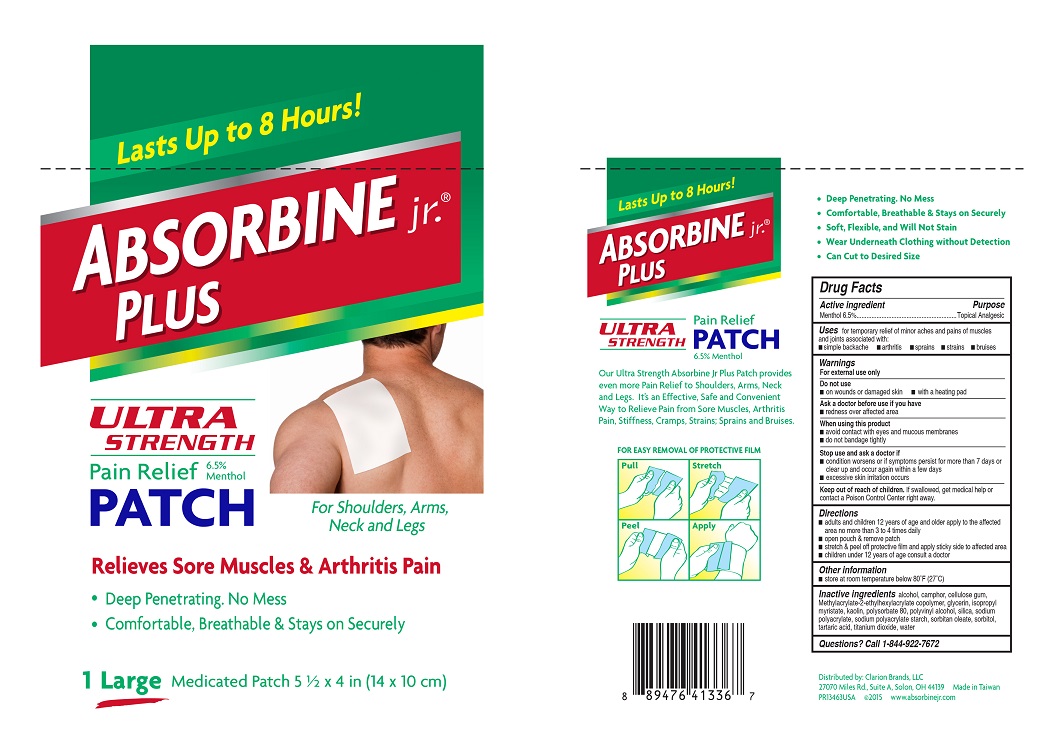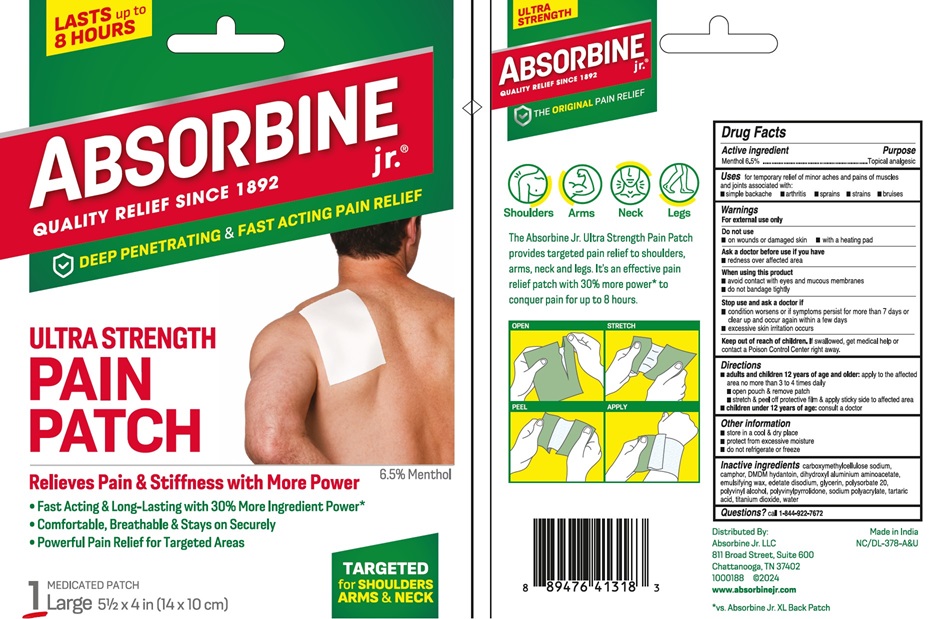 DRUG LABEL: ABSORBINE JR PLUS ULTRA STRENGTH PAIN
NDC: 69693-413 | Form: PATCH
Manufacturer: Clarion Brands, LLC
Category: otc | Type: HUMAN OTC DRUG LABEL
Date: 20251223

ACTIVE INGREDIENTS: MENTHOL 6500 mg/1 h
INACTIVE INGREDIENTS: ALCOHOL; CAMPHOR (SYNTHETIC); CARBOXYMETHYLCELLULOSE SODIUM, UNSPECIFIED FORM; GLYCERIN; ISOPROPYL MYRISTATE; KAOLIN; POLYSORBATE 80; POLYVINYL ALCOHOL, UNSPECIFIED; SILICON DIOXIDE; SORBITAN MONOOLEATE; SORBITOL; TARTARIC ACID; TITANIUM DIOXIDE; WATER

Drug Facts

Active Ingredient

Menthol 6.5%

Purpose

Topical Analgesic

Uses

For temporary relief of minor aches and pains of muscles and joints associated with:

- simple backache
- arthritis
- sprains
- strains
- bruises

Warnings

For external use only

Do not use

- on wounds or damaged skin
- with a heating pad

Ask a doctor before use if you have

- redness over affected area

When using this product

- avoid contact with eyes and mucous membranes
- do not bandage tightly

Stop use and ask a doctor if

- condition worsens or if symptoms persist for more than 7 days or clear up and occur again within a few days
- excessive skin irration occurs

Keep out of reach of children.

If swallowed, get medical help or contact a Poison Control Center right away.

Directions

- adults and children 12 years of age and older apply to the affected area no more than 3 to 4 times daily
- open pouch & remove patch
- stretch & peel off protective film and apply sticky side to affected area
- children under 12 years of age consult a doctor

Other information

- store at room temperature below 80°F (27°C)

Inactive ingredients

alcohol, camphor, cellulose gum, Methylacrylate-2-ethylhexyacrylate copolymer, glycerin, isopropyl myristate, kaolin, polysorbate 80, polyvinyl alcohol, silica, sodium polyacrylate, sodium polyacrylate starch, sorbitan oleate, sorbitol, tartaric acid, titanium dioxide, water

PRINCIPAL DISPLAY PANEL

Lasts up to 8 Hours!
ABSORBINE jr.®PLUS
ULTRA STRENGTH
Pain Relief PATCH
6.5% Menthol
For Shoulders, Arms, Neck and Legs
Relieves Sore Muscles & Arthritis Pain
● Deep Penetrating. No Mess
● Comfortable, Breathable & Stays on Securely
1 LargeMedicated Patch 5 ½ x 4 in (14 x 10 cm)
Our Ultra Strength Absorbine Jr Plus Patch provides even more Pain Relief to Shoulders, Arms, Neck and Legs. It's an Effective, Safe and Convenient Way to Relieve Pain from Sore Muscles, Arthritis Pain, Stiffness, Cramps, Strains; Sprains and Bruises.
FOR EASY REMOVAL OF PROTECTIVE FILM
Pull
Stretch
Peel
Apply
● Deep Penetrating. No Mess
● Comfortable, Breathable & Stays on Securely
● Soft, Flexible, and Will Not Stain
● Wear Underneath Clothing without Detection
● Can Cut to Desired Size
Distributed by: Clarion Brands, LLC
27070 Miles Rd., Suite A, Solon, OH 44139 Made in Taiwan
PR13463USA ©2015 www.absorbinejr.com

Lasts up to 8 Hours!
ABSORBINE jr.®
QUALITY RELIEF SINCE 1892
DEEP PENETRATING & FAST ACTING PAIN RELIEF
ULTRA STRENGTH
PAIN
PATCH
6.5% Menthol
Relieves Pain & Stiffness with More Power
● Fast Acting & Long-Lasting with 30% More Ingredient Power*
● Comfortable, Breathable & Stays on Securely
● Powerful Pain Relief for Targeted Areas
Medicated Patch
1 Large5 ½ x 4 in (14 x 10 cm)
TARGETED
for SHOULDERS
ARMS& NECK
ULTRA
STRENGTH
ABSORBINE jr.®
QUALITY RELIEF SINCE 1892
THE ORIGINALPAIN RELIEF
● Shoulders
● Arms
● Neck
● Legs
The Absorbine Jr. Ultra Strength Pain Patch
provides targeted pain relief to shoulders,
arms, neck and legs. It’s an effective pain
relief patch with 30% more power* to
conquer pain for up to 8 hours.
Distributed by:
Absorbine Jr. LLC
811 Broad Street, Suite 600
Chattanooga, TN 37402
1000188 @2024
www.absorbinejr.com
Made in India
NC/DL-378-A&U
*vs. Absorbine Jr. XL Back Patch